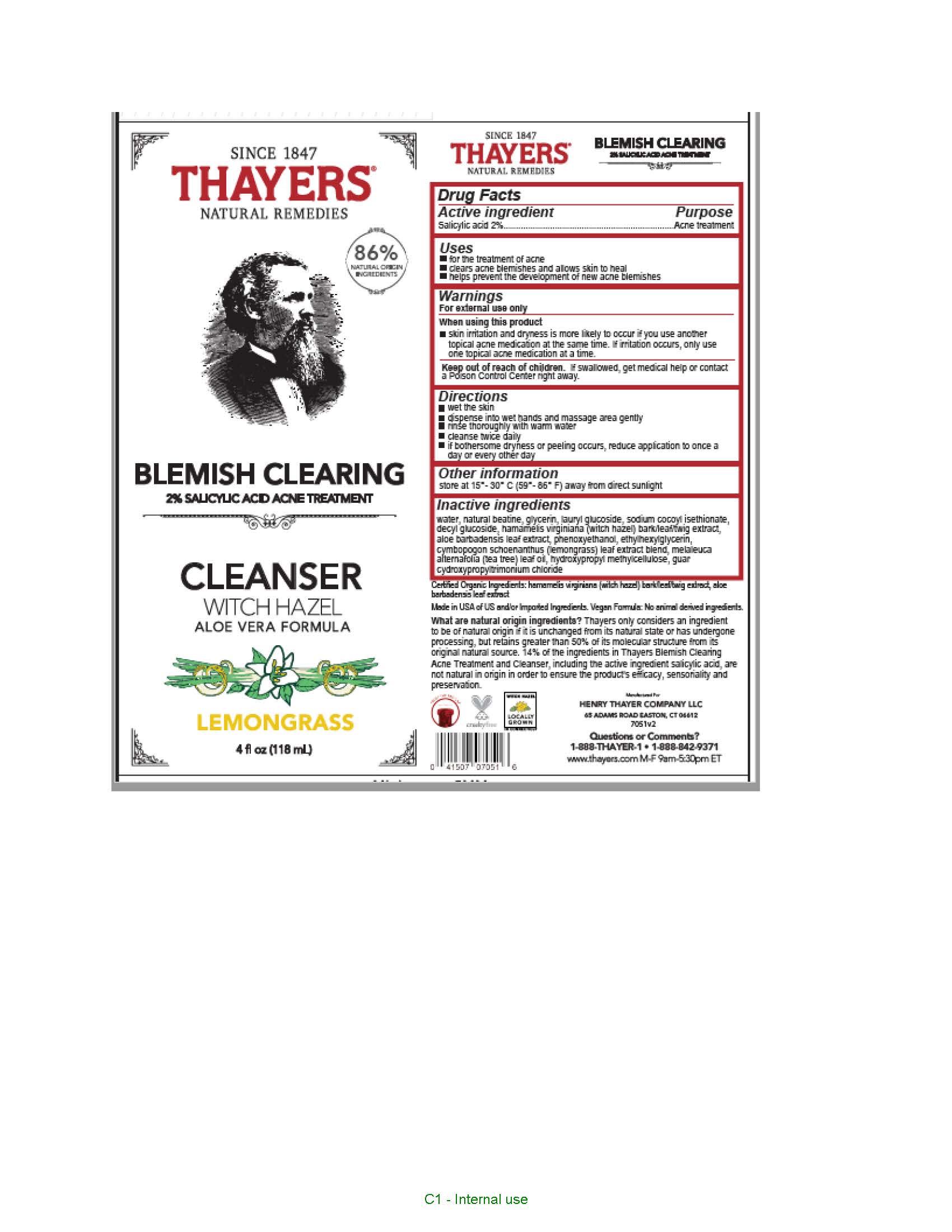 DRUG LABEL: Thayers Since 1847 Natural Remedies Blemish Clearing Witch Hazel Aloe Vera Formula Cleanser
NDC: 49967-051 | Form: GEL
Manufacturer: L'Oreal USA Products Inc
Category: otc | Type: HUMAN OTC DRUG LABEL
Date: 20231227

ACTIVE INGREDIENTS: SALICYLIC ACID 20 mg/1 mL
INACTIVE INGREDIENTS: WATER; GLYCERIN; LAURYL GLUCOSIDE; SODIUM COCOYL ISETHIONATE; DECYL GLUCOSIDE; HAMAMELIS VIRGINIANA TOP; ALOE VERA LEAF; PHENOXYETHANOL; ETHYLHEXYLGLYCERIN; TEA TREE OIL; HYPROMELLOSE, UNSPECIFIED

Drug Facts

Active ingredient

Salicylic acid 2%

Purpose

Acne treatment

Uses

• for the treatment of acne
• clears acne blemishes and allows skin to heal
• helps prevent the development of new acne blemishes

Warnings

For external use only

When using this product

skin irritation and dryness is more likely to occur if you use another topical acne medication at the same time. If irritation occurs, only use one topical acne medication at a time.

Keep out of reach of children.

If swallowed, get medical help or contact a Poison Control Center right away.

Directions

- wet the skin
- dispense into wet hands and massage area gently
- rinse thoroughly with warm water
- cleanse twice daily
- if bothersome dryness or peeling occurs, reduce application to once a day or every other day

Other information

store at 15°-30° C (59°-86° F) away from direct sunlight

Inactive ingredients

water, natural beatine, glycerin, lauryl glucoside, sodium cocoyl isethionate, decyl glucoside, hamamelis virginiana (witch hazel) bark/leaf/twig extract, aloe barbadensis leaf extract, phenoxyethanol, ethylhexylglycerin, cymbopogon schoenanthus (lemongrass) leaf extract blend, melaleuca
alternafolia (tea tree) leaf oil, hydroxypropyl methylcellulose, guar cydroxypropyltrimonium chloride